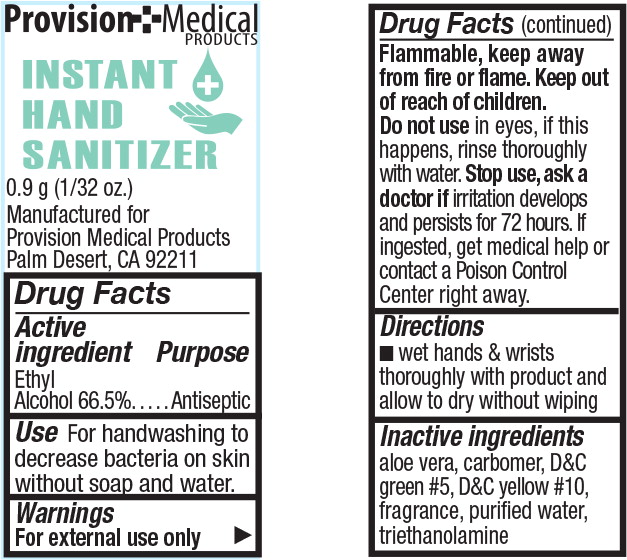 DRUG LABEL: Instant Hand Sanitizer
NDC: 69103-3554 | Form: GEL
Manufacturer: Provision Medical 
Category: otc | Type: HUMAN OTC DRUG LABEL
Date: 20150316

ACTIVE INGREDIENTS: alcohol 665 mL/1 g
INACTIVE INGREDIENTS: aloe; carbomer interpolymer type a (allyl sucrose crosslinked); d&c green no. 5; d&c yellow no. 10; water; trolamine

Drug Facts

Active ingredient

Ethyl

Alcohol 66.5%

Purpose

Antiseptic

Use

For handwashing to decrease bacteria on skin without soap and water.

Warnings

For external use only

Flammable, keep away from fire or flame.

Do not use in eyes, if this happens, rinse thoroughly with water.

Stop use, ask a doctor if irritation develops and persists for 72 hours. If ingested, get medical help or contact a Poison Control Center right away.

Directions

- wet hands & wrists thoroughly with product and allow to dry without wiping

Inactive ingredients

aloe vera, carbomer, D&C green #5, D&C yellow #10, fragrance, purified water, triethanolamine

Principal Display Panel - 0.9g Packet Label

Provision Medical PRODUCTS

INSTANT

HAND

SANITIZER

0.9 g (1/32 oz.)

Manufactured for

Provision Medical Products

Palm Desert, CA 92211